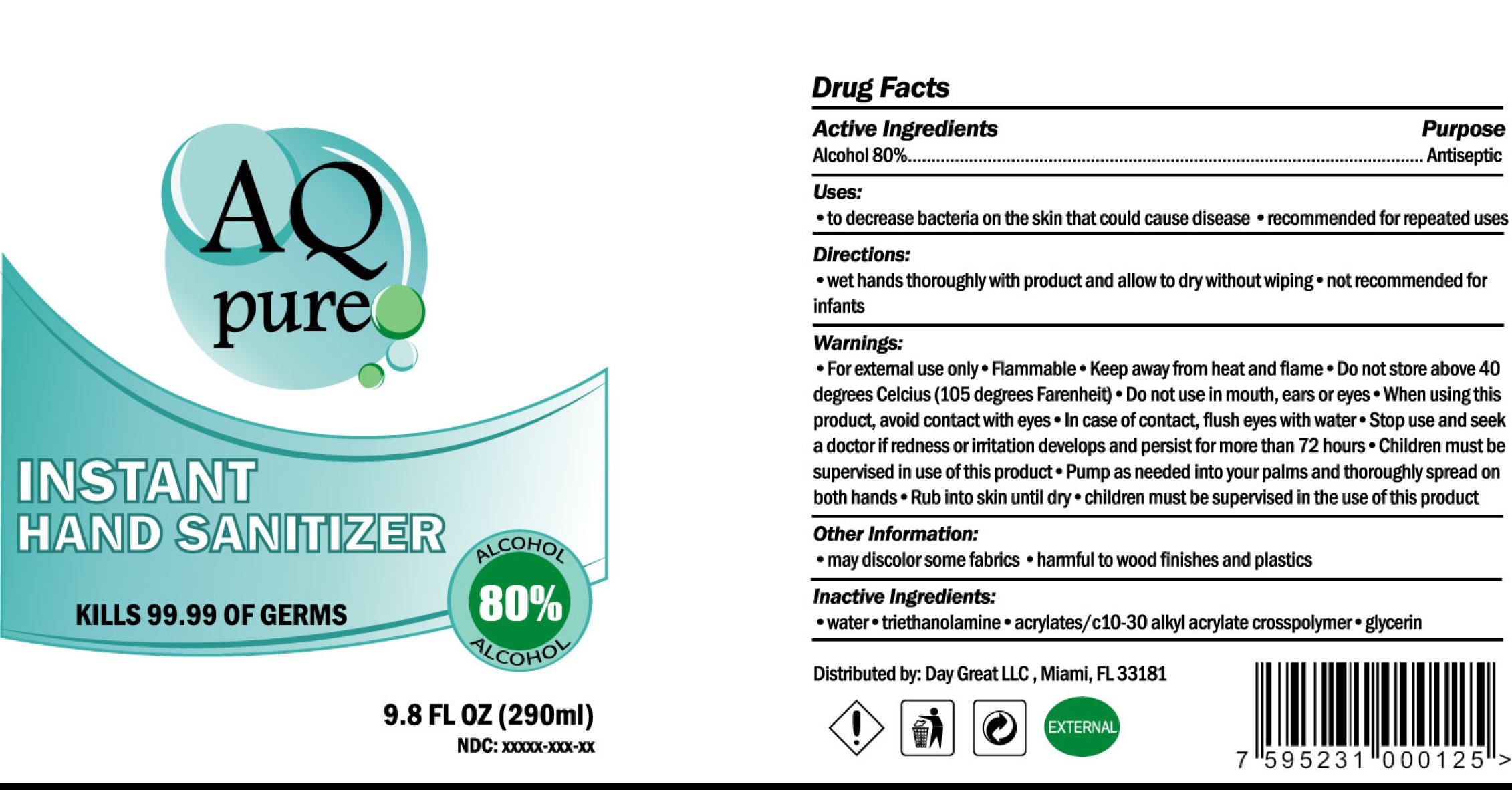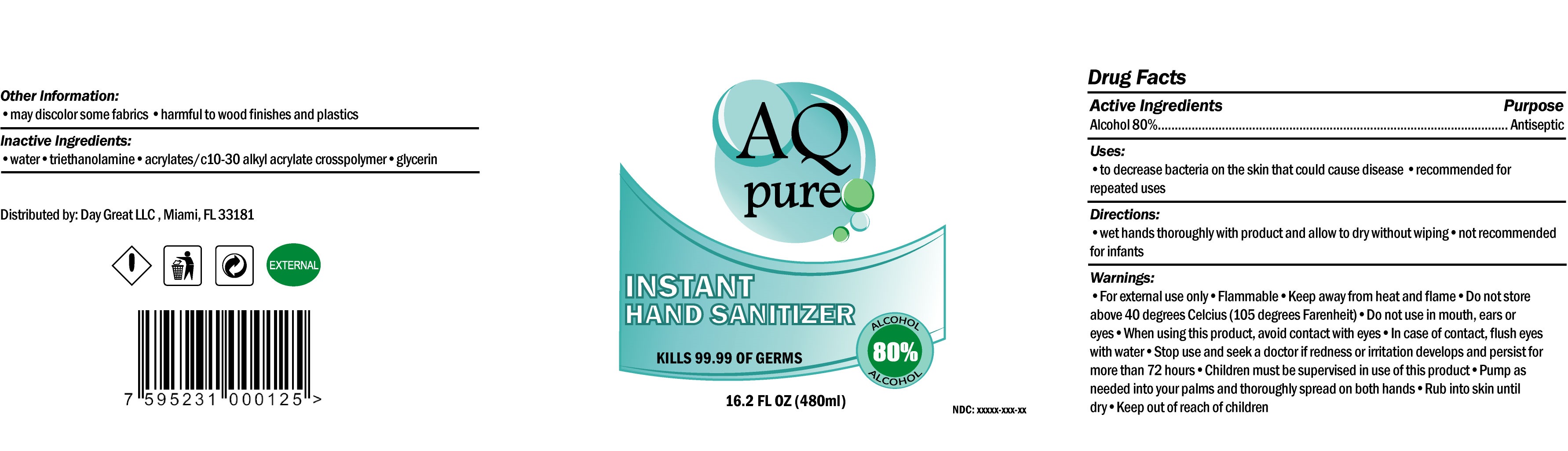 DRUG LABEL: AQ pure Instant Hand Sanitizer
NDC: 79333-001 | Form: GEL
Manufacturer: DAY GREAT LLC
Category: otc | Type: HUMAN OTC DRUG LABEL
Date: 20200731

ACTIVE INGREDIENTS: ALCOHOL 0.8 mL/1 mL
INACTIVE INGREDIENTS: CARBOMER INTERPOLYMER TYPE A (ALLYL SUCROSE CROSSLINKED); WATER; TROLAMINE; GLYCERIN

AQ pure Instant Hand Sanitizer

Active Ingredients

Alcohol 80%

Purpose

Antiseptic

Uses:

- wet hands bacteria on the skin that could disease
- recommended for repeated uses

Directions:

- wet hands thoroughly with product and allow to dry without wiping
- not recommende for infants

Warnings:

- For external use only
- Flammable
- Keep away from heat and flame
- Do not store above 40 degrees Celcius (15 degrees Farenheit)

Do not use

- in mouth, ears or eyes

When using this product,

- avoid contact with eyes
- In case of contact, flush eyes with water

Stop use and seek a doctor

- if redness or irritation develops and persist for more than 72 hours
- Children must be supervise in use of this product
- Pump as needed into your palms and thoroughly spread on both hands
- Rub in to skin until dry

Keep out of reach of children

- children must be supervised in the use of this product

Other Information:

- may discolor some fabrics
- harmful to wood finishes and plastics

Inactive Ingredients:

- water
- triethanolamine
- acrylates/c 10-30 alkyl crosspolymer
- glycerin